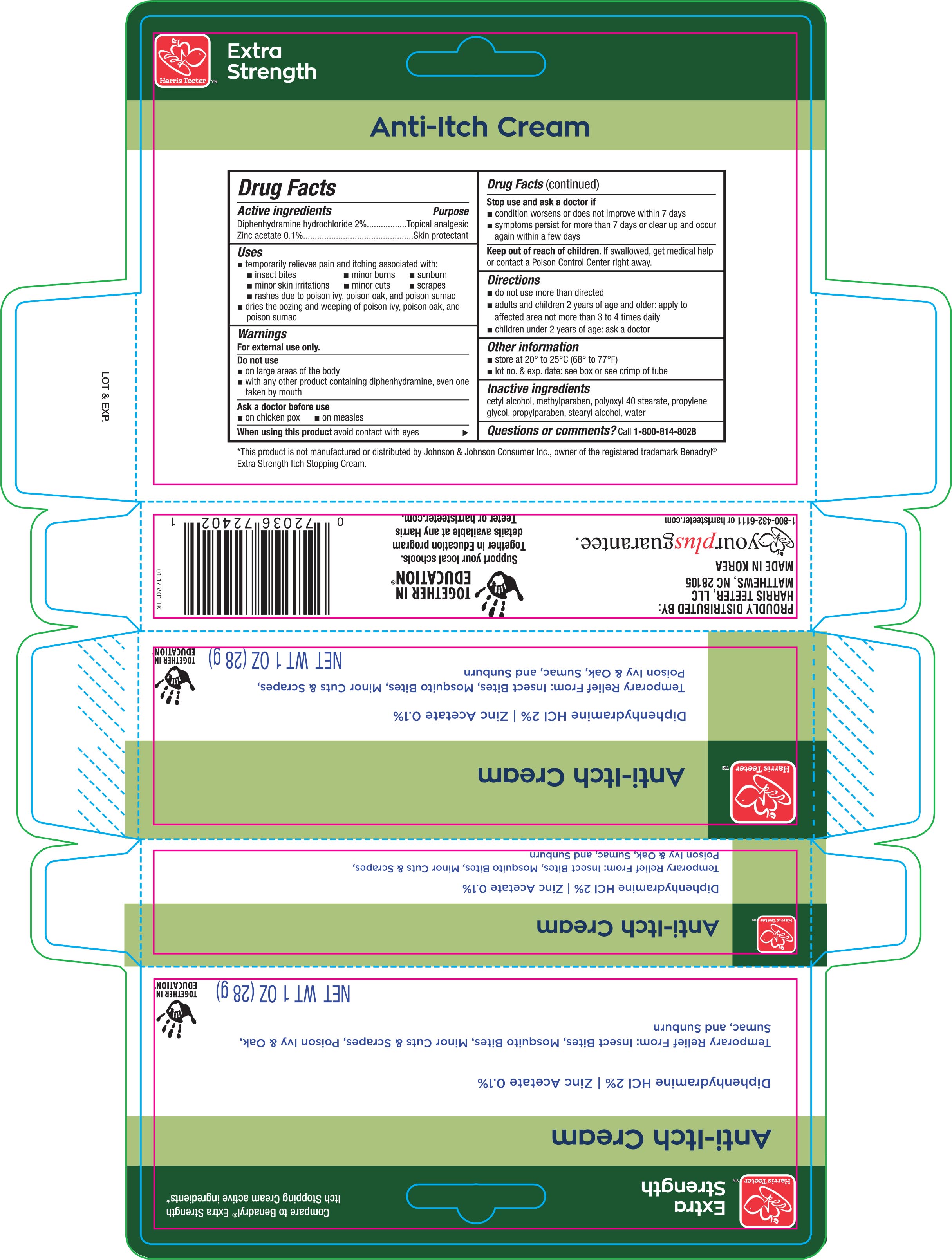 DRUG LABEL: Harris Teeter Anti-Itch
NDC: 72036-402 | Form: CREAM
Manufacturer: Harris Teeter
Category: otc | Type: HUMAN OTC DRUG LABEL
Date: 20170421

ACTIVE INGREDIENTS: DIPHENHYDRAMINE HYDROCHLORIDE 20 mg/1 g; ZINC ACETATE 1 mg/1 g
INACTIVE INGREDIENTS: CETYL ALCOHOL; METHYLPARABEN; POLYOXYL 40 STEARATE; PROPYLENE GLYCOL; PROPYLPARABEN; STEARYL ALCOHOL; WATER

Active ingredients Purpose

Diphenhydramine hydrochloride 2%.........Topical analgesic

Zinc acetate 0.1%...................................Skin protectant

Uses

- temporarily relieves pain and itching associated with:
- insect bites
- minor burns
- sunburn
- minor skin irritations
- minor cuts
- scrapes
- rashes due to poison ivy, poison oak, and poison sumac
- dries the oozing and weeping of poison ivy, poison oak, and poison sumac

Warnings

For external use only.

Do not use

- on large areas of the body
- with any other product containing diphenhydramine, even one take by mouth

Ask a doctor before use

- on chicken pox
- on measles

When using this product

avoid contact with eyes

Stop use and ask a doctor if

- conditions worsens or does not improve within 7 days
- symptoms persist for more than 7 days or clear up and occur again within a few days

Keep out of reach of children.

If swallowed, get medical help or contact a Poison Control Center right away.

Directions

- do not use more than directed
- adults and children 2 years of age and older: apply to affected area not more than 3 to 4 times daily
- children under 2 years of age: ask a doctor

Other information

- store at 20° to 25°C (68° to 77°F)
- lot no. & exp. date: see box or see crimp of tube

Inactive ingredients

cetyl alcohol, methylparaben, polyoxyl 40 stearate, propylene glycol, propylparaben, stearyl alcohol, water

DOSAGE AND ADMINISTRATION

PROUDLY DISTRIBUTED BY:

HARRIS TEETER, LLC

MATTHEWS, NC 28105

MADE IN KOREA